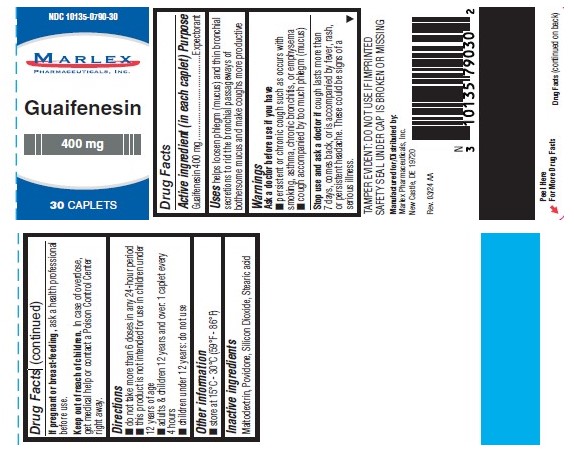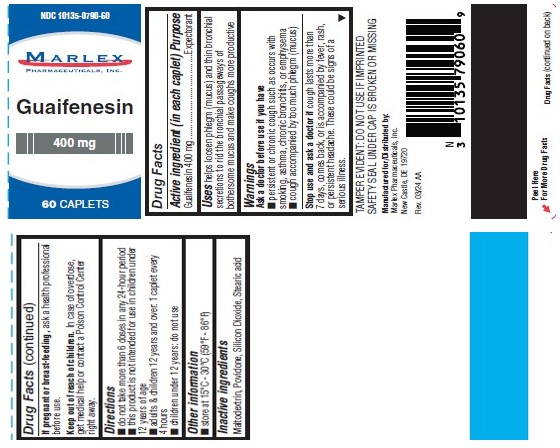 DRUG LABEL: Guaifenesin 400mg
NDC: 10135-790 | Form: TABLET
Manufacturer: Marlex Pharmaceuticals Inc
Category: otc | Type: HUMAN OTC DRUG LABEL
Date: 20251113

ACTIVE INGREDIENTS: GUAIFENESIN 400 mg/1 1
INACTIVE INGREDIENTS: SILICON DIOXIDE; MALTODEXTRIN; POVIDONE; STEARIC ACID

Guaifenesin 400mg

GUAIFENESIN 400 MG CAPLETS

Marlex Pharmaceuticals, Inc.

----------

Drug Fact

Active ingredient (in each tablet)

Guaifenesin 400mg

Purpose

Expectorant

Guaifenesin 400 mg Caplets

Uses

helps loosen phlegm (mucus) and thin bronchial secretions to rid the bronchial passageway of bothersome mucus and make coughs more productive

Warnings

Ask a doctor before use if you have

- Persistent or chronic cough such as occurs with smoking, asthma, chronic bronchitis, or emphysema
- Cough accompanied by too much phlegm (mucus)

Stop use and ask a doctor if

cough last more than 7 days, comes back or is accompanied by fever, rash, or persistent headache. These could be signs of a serious illness.

TAMPER EVIDENT: DO NOT USE IF IMPRINTED SAFETY SEAL UNDER CAP IS BROKEN OR MISSING.

If pregnant or breast- feeding,

ask a health professional before use.

Keep out of reach of children.

In case of overdose, get medical help or contact a Poison Control Center right away.

Directions:

- Do not take more than 6 doses in any 24-hour period.
- This product is not intended for use in children under 12 years of age
- Adults & children 12 years and over: 1 to 2 tablets every 4 hours
- Children under 12 years: do not use

Other Information:

- Store at 15°C-30°C (59°F-86°F)

Inactive Ingredients:

Maltodextrin, Povidone, Silicon Dioxide, Stearic acid.

Manufactured for & Distributed by:

Marlex Pharmaceuticals, Inc.

New Castle, DE 19720

Rev. 03/24 AA

PRINCIPAL DISPLAY PANEL

NDC 10135-0790-30
Guaifenesin
400 mg
30 CAPLETS

PRINCIPAL DISPLAY PANEL

NDC 10135-0790-60
Guaifenesin
400 mg
60 CAPLETS